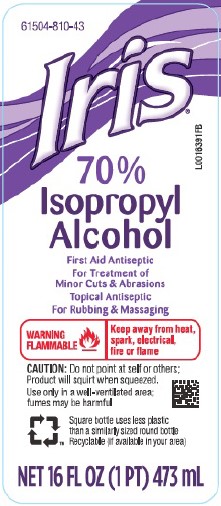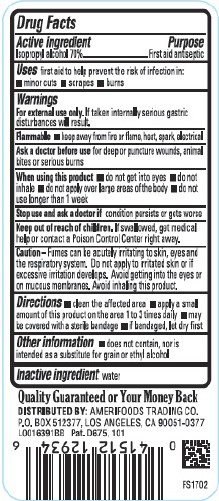 DRUG LABEL: IRIS
NDC: 61504-810 | Form: LIQUID
Manufacturer: Amerifoods Trading Co
Category: otc | Type: HUMAN OTC DRUG LABEL
Date: 20260129

ACTIVE INGREDIENTS: ISOPROPYL ALCOHOL 70 mL/100 mL
INACTIVE INGREDIENTS: WATER 30 g/100 mL

Iris 810.003/810AA
Isopropyl Alcohol 70%

Active Ingredient

Isopropyl alcohol 70%

Purpose

First aid antiseptic

Uses

helps prevent the risk of infection in:

- minor cuts
- scrapes
- burns

Warnings

For external use only. If taken internally serious gastric disturbances will result.

Flammable

- keep away from fire or flame, heat, spark, electrical

Ask a doctor before use

for deep or puncture wounds, animal bites or serious burns

When using this product

- do not get into eyes
- do not inhale
- do not apply over large areas of the body
- do not use longer than 1 week

Stop use and ask a doctor if

condition persists or gets worse

Keep out of reach of children.

If swallowed, get medical help or contact a Poison Control Center right away.

Caution

Fumes can be acutely irritating to skin, eyes and the respiratory system. Do not apply to irritated skin or if excessive irritation develops. Avoid getting into the eyes or on mucous membranes. Avoid inhaling this product.

DIRECTIONS

- clean the affected area
- apply a small amount of this product on the area 1 to 3 times daily
- may be covered with a sterile bandage
- if bandaged, let dry first

Other information

- does not contain, nor is intended as a substitute for grain or ethyl alcohol

Inactive Ingredient

water

Adverse reactions

Quality Guaranteed or Your Money Back

DISTRIBUTED BY: AMERIFOODS TRADING CO.

P. O. BOX 512377, LOS ANGELES, CA 90051-0377

Pat. D675, 101

principal display panel

61504-810-43

Iris®

70% Isopropyl Alcohol

First Aid Antiseptic

For Treatment of Minor Cuts & Abrasions

Topical Antiseptic

For Rubbing and Massaging

WARNING FLAMMABLE - Keep away from heat, spark, electrical, flame

CAUTION: Do not point at self or others; Product will squirt when squeezed.

Use only in a well-ventilated area; fumes may be harmful

NET 16 FL OZ (1 PT) 473 mL